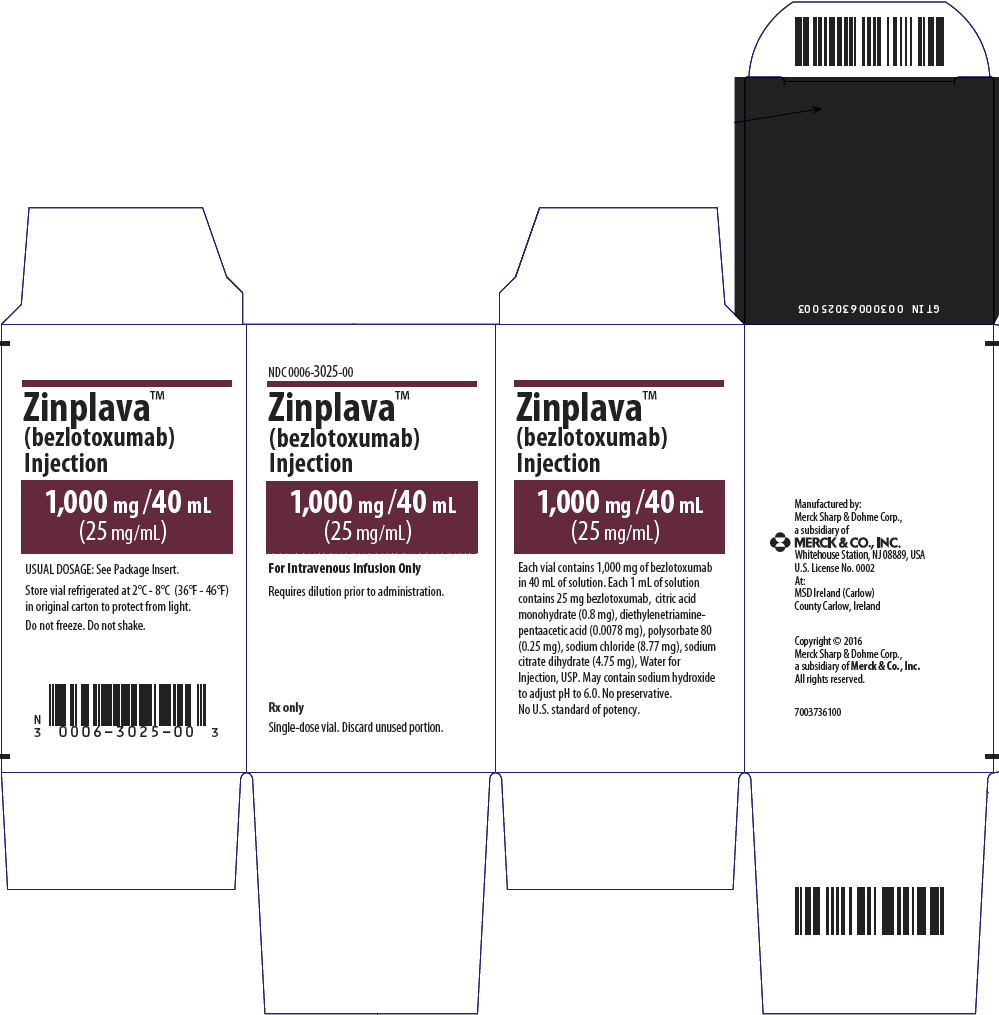 DRUG LABEL: ZINPLAVA
NDC: 0006-3025 | Form: INJECTION, SOLUTION
Manufacturer: Merck Sharp & Dohme LLC
Category: prescription | Type: HUMAN PRESCRIPTION DRUG LABEL
Date: 20241112

ACTIVE INGREDIENTS: bezlotoxumab 25 mg/1 mL
INACTIVE INGREDIENTS: CITRIC ACID MONOHYDRATE 0.8 mg/1 mL; PENTETIC ACID 0.0078 mg/1 mL; POLYSORBATE 80 0.25 mg/1 mL; SODIUM CHLORIDE 8.77 mg/1 mL; TRISODIUM CITRATE DIHYDRATE 4.75 mg/1 mL; WATER; SODIUM HYDROXIDE

HIGHLIGHTS OF PRESCRIBING INFORMATION

These highlights do not include all the information needed to use ZINPLAVA safely and effectively. See full prescribing information for ZINPLAVA.
ZINPLAVA™ (bezlotoxumab) injection, for intravenous use
Initial U.S. Approval: 2016

RECENT MAJOR CHANGES

Indications and Usage (1) | 5/2023
Dosage and Administration, Dosing Recommendations in Adults and Pediatric Patients 1 year of age and older (2.2) | 5/2023

1 INDICATIONS AND USAGE

ZINPLAVA is a human monoclonal antibody that binds to Clostridioides difficile toxin B, indicated to reduce recurrence of Clostridioides difficile infection (CDI) in adults and pediatric patients 1 year of age and older who are receiving antibacterial drug treatment for CDI and are at a high risk for CDI recurrence. (1)

Limitation of Use:

ZINPLAVA is not indicated for the treatment of CDI. ZINPLAVA is not an antibacterial drug. ZINPLAVA should only be used in conjunction with antibacterial drug treatment of CDI. (1)

2 DOSAGE AND ADMINISTRATION

- Administer ZINPLAVA during antibacterial drug treatment for CDI. (2.1)
- The recommended dose is a single dose of 10 mg/kg administered as an intravenous infusion over 60 minutes. (2.2)
- Dilute prior to intravenous infusion. Administer via a low-protein binding 0.2 micron to 5 micron in-line or add-on filter. See Full Prescribing Information for dilution and administration instructions. (2.3)

3 DOSAGE FORMS AND STRENGTHS

Injection: 1,000 mg/40 mL (25 mg/mL) solution in a single-dose vial. (3)

4 CONTRAINDICATIONS

None (4)

5 WARNINGS AND PRECAUTIONS

Heart Failure: Was reported more commonly in ZINPLAVA-treated patients with a history of congestive heart failure (CHF) in Trial 1 and Trial 2. In patients with a history of CHF, ZINPLAVA should be reserved for use when the benefit outweighs the risk. (5.1)

6 ADVERSE REACTIONS

- Adult Patients: The most common adverse reactions (reported in ≥4% of adult patients) included nausea, pyrexia, and headache. (6.1)
- Pediatric Patients: The most common adverse reactions (reported in >10% of pediatric patients) were pyrexia and headache (6.1)

To report SUSPECTED ADVERSE REACTIONS, contact Merck Sharp & Dohme LLC at 1-877-888-4231 or FDA at 1-800-FDA-1088 or www.fda.gov/medwatch .

FULL PRESCRIBING INFORMATION

1 INDICATIONS AND USAGE

ZINPLAVA™ is indicated to reduce recurrence of Clostridioides difficile infection (CDI) in adults and pediatric patients 1 year of age and older who are receiving antibacterial drug treatment for CDI and are at a high risk for CDI recurrence.

Limitation of Use:

ZINPLAVA is not indicated for the treatment of CDI. ZINPLAVA is not an antibacterial drug. ZINPLAVA should only be used in conjunction with antibacterial drug treatment of CDI. [See Dosage and Administration (2.1).]

2 DOSAGE AND ADMINISTRATION

2.1 Important Administration Instructions

Administer ZINPLAVA during antibacterial drug treatment for CDI.

2.2 Dosing Recommendations in Adults and Pediatric Patients 1 year of age and older

The recommended dose of ZINPLAVA is a single dose of 10 mg/kg administered as an intravenous infusion over 60 minutes. The safety and efficacy of repeat administration of ZINPLAVA in patients with CDI have not been studied.

2.3 Preparation and Administration

Preparation of Diluted Solution

- ZINPLAVA must be diluted prior to intravenous infusion.
- Prepare the diluted solution immediately after removal of the vial(s) from refrigerated storage, or the vial(s) may be stored at room temperature protected from light for up to 24 hours prior to preparation of the diluted solution.
- Inspect vial contents for discoloration and particulate matter prior to dilution. ZINPLAVA is a clear to moderately opalescent, colorless to pale yellow solution. Do not use the vial if the solution is discolored or contains visible particles.
- Do not shake the vial.
- Withdraw the required volume from the vial(s) based on the patient's weight (in kg) and transfer into an intravenous bag containing either 0.9% Sodium Chloride Injection, USP or 5% Dextrose Injection, USP to prepare a diluted solution with a final concentration ranging from 1 mg/mL to 10 mg/mL. Mix diluted solution by gentle inversion. Do not shake.
- Discard vial(s) and all unused contents.

Storage of Diluted Solution

- The product does not contain preservative. The diluted solution of ZINPLAVA may be stored either at room temperature for up to 16 hours or under refrigeration at 2°C to 8°C (36°F to 46°F) for up to 24 hours. If refrigerated, allow the intravenous bag to come to room temperature prior to use.
- These time limits include storage of the infusion solution in the intravenous bag through the duration of infusion.
- Do not freeze the diluted solution.

Administration

- Administer the diluted solution as an intravenous infusion over 60 minutes using a sterile, non-pyrogenic, low-protein binding 0.2 micron to 5 micron in-line or add-on filter.
- The diluted solution can be infused via a central line or peripheral catheter. Do not administer ZINPLAVA as an intravenous push or bolus.
- Do not co-administer other drugs simultaneously through the same infusion line.

3 DOSAGE FORMS AND STRENGTHS

Injection: 1,000 mg/40 mL (25 mg/mL) clear to moderately opalescent, colorless to pale yellow solution in a single-dose vial.

4 CONTRAINDICATIONS

None.

5 WARNINGS AND PRECAUTIONS

5.1 Heart Failure

Heart failure was reported more commonly in Trial 1 and Trial 2 in ZINPLAVA-treated patients compared to placebo-treated patients. These adverse reactions occurred primarily in patients with underlying congestive heart failure (CHF). In patients with a history of CHF, 12.7% (15/118) of ZINPLAVA-treated patients and 4.8% (5/104) of placebo-treated patients had the serious adverse reaction of heart failure during the 12-week study period [see Adverse Reactions (6.1)]. Additionally, in patients with a history of CHF, there were more deaths in ZINPLAVA-treated patients, 19.5% (23/118) than in placebo-treated patients, 12.5% (13/104) during the 12-week study period. The causes of death varied and included cardiac failure, infections, and respiratory failure.

In patients with a history of CHF, ZINPLAVA should be reserved for use when the benefit outweighs the risk.

6 ADVERSE REACTIONS

6.1 Clinical Trials Experience

Because clinical trials are conducted under widely varying conditions, adverse reaction rates observed in the clinical trials of a drug cannot be directly compared to rates in the clinical trials of another drug and may not reflect the rates observed in practice.

Clinical Trials Experience in Adults

The safety of ZINPLAVA was evaluated in two placebo-controlled Phase 3 trials (Trial 1 n=390 and Trial 2 n=396). Patients received a single 10 mg/kg intravenous infusion of ZINPLAVA and concomitant standard of care (SoC) antibacterial drugs (metronidazole, vancomycin or fidaxomicin) for CDI. Adverse reactions reported within the first 4 weeks after ZINPLAVA was administered are described for the pooled Phase 3 trial population of 786 patients. The median age of patients receiving ZINPLAVA was 65 years (range 18 to 100), 50% were age 65 years or older, 56% were female, and 83% were white.

Serious Adverse Reactions in Adults

Serious adverse reactions occurring within 12 weeks following infusion were reported in 29% of ZINPLAVA-treated patients and 33% of placebo-treated patients. Heart failure was reported as a serious adverse reaction in 2.3% of the ZINPLAVA-treated patients and 1.0% of the placebo-treated patients [see Warnings and Precautions (5.1)].

One patient discontinued the ZINPLAVA infusion due to ventricular tachyarrhythmia that occurred 30 minutes after the start of the infusion.

Mortality rates were 7.1% and 7.6% in ZINPLAVA-treated patients and placebo-treated patients, respectively, during the 12-week follow-up period.

Most Common Adverse Reactions in Adults

The most common adverse reactions following treatment with ZINPLAVA (reported in ≥4% of patients within the first 4 weeks of infusion and with a frequency greater than placebo) were nausea, pyrexia, and headache (see Table 1).

Table 1: Adverse Reactions Reported in ≥4% of ZINPLAVA-Treated Patients with CDI and at a Frequency Greater than Placebo in Trial 1 and Trial 2 [All patients as treated population, defined as all randomized patients who received a dose of study medication, by treatment received] , [Adverse reactions reported within 4 weeks of administration of ZINPLAVA or placebo]
Adverse Reaction | ZINPLAVA with SoC [SoC = Standard of Care antibacterial drugs (metronidazole or vancomycin or fidaxomicin) for CDI] N=786 % | Placebo with SoC N=781 %
Gastrointestinal disorders
Nausea | 7% | 5%
General disorders and administration site conditions
Pyrexia | 5% | 3%
Nervous system disorders
Headache | 4% | 3%

Infusion Related Adverse Reactions in Adults

Overall, 10% of ZINPLAVA-treated patients experienced one or more infusion specific adverse reactions on the day of, or the day after, the infusion compared to 8% of placebo-treated patients. Infusion specific adverse reactions reported in ≥0.5% of patients receiving ZINPLAVA and at a frequency greater than placebo were nausea (3%), fatigue (1%), pyrexia (1%), dizziness (1%), headache (2%), dyspnea (1%) and hypertension (1%). Of these patients, 78% and 20% of patients experienced mild and moderate adverse reactions, respectively. These reactions resolved within 24 hours following onset.

Clinical Trial Experience in Pediatric Patients

The safety and pharmacokinetics of ZINPLAVA in pediatric patients 1 year of age and older were evaluated in a randomized, double-blind, placebo-controlled, multi-center trial (Trial 3). Enrolled patients had a diagnosis of CDI and received SoC (vancomycin, metronidazole, or fidaxomicin) for the baseline CDI episode. In this trial, 143 patients were randomized and treated, of whom 107 received a single infusion of ZINPLAVA (10 mg/kg) and 36 received a placebo infusion. Of these randomized patients, 58% were 1 to <12 years of age, 52% were male, 80% were white, and 7% were multi-racial. The majority (94%) of patients had one or more risk factors for CDI recurrence. [See Clinical Pharmacology (12.3).]

The adverse reactions observed in pediatric patients were comparable to those observed in adult patients. Five of 107 pediatric patients (5%) receiving ZINPLAVA and one of 36 pediatric patients receiving placebo (3%) died in Trial 3. There were no treatment discontinuations due to adverse reactions. The most common adverse reactions occurring in greater than 10% of pediatric patients treated with ZINPLAVA were pyrexia (19 patients, 18%) and headache (15 patients, 14%). One ZINPLAVA-treated pediatric patient (1%) experienced an infusion-related adverse reaction.

7 DRUG INTERACTIONS

Since ZINPLAVA is eliminated by catabolism, no metabolic drug-drug interactions are expected [see Clinical Pharmacology (12.3)].

8 USE IN SPECIFIC POPULATIONS

8.1 Pregnancy

Risk Summary

Adequate and well controlled studies with ZINPLAVA have not been conducted in pregnant women. No animal reproductive and developmental studies have been conducted with bezlotoxumab.

The background risk of major birth defects and miscarriage for the indicated population is unknown; however, the background risk in the U.S. general population of major birth defects is 2-4% and of miscarriage is 15-20% of clinically recognized pregnancies.

8.2 Lactation

Risk Summary

There is no information regarding the presence of bezlotoxumab in human milk, the effects on the breast-fed infant, or the effects on milk production.

The developmental and health benefits of breastfeeding should be considered along with the mother's clinical need for ZINPLAVA and any potential adverse effects on the breastfed child from ZINPLAVA or from the underlying maternal condition.

8.4 Pediatric Use

The safety and effectiveness of ZINPLAVA to reduce recurrence of CDI have been established in pediatric patients 1 year of age and older. Use of ZINPLAVA in pediatric patients 1 year of age and older is supported by evidence from adequate and well-controlled trials in adults with additional pharmacokinetic and safety data in pediatric patients aged 1 year and older. The adverse reactions and the pharmacokinetics observed in pediatric patients were comparable to that observed in adult patients [see Adverse Reactions (6.1) and Clinical Pharmacology (12.3)].

The safety and effectiveness of ZINPLAVA have not been established in pediatric patients younger than 1 year of age.

8.5 Geriatric Use

Of the 786 patients treated with ZINPLAVA, 50% were 65 years of age and over, and 27% were 75 years of age and over. No overall differences in safety and efficacy were observed between these subjects and younger subjects [see Clinical Studies (14)]. No dose adjustment is necessary for patients ≥65 years of age [see Clinical Pharmacology (12.3)].

10 OVERDOSAGE

There is no clinical experience with overdosage of ZINPLAVA. In case of overdose, patients should be closely monitored for signs or symptoms of adverse reactions, and appropriate symptomatic treatment should be instituted.

11 DESCRIPTION

Bezlotoxumab is a human monoclonal antibody that binds to C. difficile toxin B and neutralizes its effects. Bezlotoxumab is an IgG1 immunoglobulin with an approximate molecular weight of 148.2 kDa.

ZINPLAVA (bezlotoxumab) Injection is a sterile, preservative-free, clear to moderately opalescent, colorless to pale yellow solution that requires dilution for intravenous infusion. The product is provided in a 50 mL vial that contains 1000 mg of bezlotoxumab in 40 mL of solution. Each mL of solution contains bezlotoxumab (25 mg), citric acid monohydrate (0.8 mg), diethylenetriaminepentaacetic acid (0.0078 mg), polysorbate 80 (0.25 mg), sodium chloride (8.77 mg), sodium citrate dihydrate (4.75 mg), and Water for Injection, USP. The vial may contain sodium hydroxide to adjust the pH to 6.0.

12 CLINICAL PHARMACOLOGY

12.1 Mechanism of Action

ZINPLAVA (bezlotoxumab) is a human monoclonal antibody that binds to C. difficile toxin B and neutralizes its effects [see Microbiology (12.4)].

12.3 Pharmacokinetics

The pharmacokinetics of bezlotoxumab were studied in 1515 adult CDI patients in two Phase 3 trials (Trial 1 and Trial 2). Based on a population PK analysis, the geometric mean (%CV) clearance of bezlotoxumab was 0.317 L/day (41%), with a mean volume of distribution of 7.33 L (16%), and elimination half-life (t½) of approximately 19 days (28%). After a single intravenous dose of 10 mg/kg ZINPLAVA, geometric mean AUC0-INF and Cmax were 53000 mcg∙h/mL and 185 mcg/mL, respectively, in the adult patients with CDI. The clearance of bezlotoxumab increased with increasing body weight; the resulting exposure differences are adequately addressed by the administration of a weight-based dose. Bezlotoxumab is eliminated by catabolism.

Specific Populations

Gender, Race, Ethnicity, and Co-Morbid Conditions

The following factors had no clinically meaningful effect on the exposure of bezlotoxumab in adults: gender, race, ethnicity, and presence of co-morbid conditions.

Patients with Renal Impairment

The effect of renal impairment on the pharmacokinetics of bezlotoxumab was evaluated in adult patients with mild (eGFR 60 to <90 mL/min/1.73 m^2), moderate (eGFR 30 to <60 mL/min/1.73 m^2), or severe (eGFR 15 to <30 mL/min/1.73 m^2) renal impairment, or with end stage renal disease (eGFR <15 mL/min/1.73 m^2), as compared to adult patients with normal (eGFR ≥90 mL/min/1.73 m^2) renal function. No clinically meaningful differences in the exposure of bezlotoxumab were found between adult patients with renal impairment and adult patients with normal renal function.

Patients with Hepatic Impairment

The effect of hepatic impairment on the pharmacokinetics of bezlotoxumab was evaluated in adult patients with hepatic impairment (defined as having two or more of the following: [1] albumin ≤3.1 g/dL; [2] ALT ≥2× ULN; [3] total bilirubin ≥1.3× ULN; or [4] mild, moderate or severe liver disease as reported by the Charlson Co-morbidity Index), as compared to adult patients with normal hepatic function. No clinically meaningful differences in the exposure of bezlotoxumab were found between adult patients with hepatic impairment and adult patients with normal hepatic function.

Geriatric Patients

The effect of age on the pharmacokinetics of bezlotoxumab was evaluated in patients ranging from 18 to 100 years of age. No clinically meaningful differences in the exposure of bezlotoxumab were found between patients 65 years and older and patients under 65 years of age.

Pediatric Patients

The pharmacokinetics of bezlotoxumab were studied in 90 pediatric patients (1 year to less than 18 years) and after a single intravenous dose of 10 mg/kg ZINPLAVA, geometric mean (%CV) AUC0-INF and Cmax were 47,900 (35.9) mcg·h/mL and 139 (32.4) mcg/mL, respectively.

There is no clinically meaningful relationship between bezlotoxumab exposure and body weight following weight-based dosing of ZINPLAVA in pediatric patients.

Drug Interaction Studies

Because bezlotoxumab is eliminated by catabolism, no metabolic drug-drug interactions are expected.

12.4 Microbiology

Mechanism of Action

Bezlotoxumab is a human monoclonal antibody that binds C. difficile toxin B with an equilibrium dissociation constant (Kd) of <1×10^-9M. Bezlotoxumab inhibits the binding of toxin B and prevents its effects on mammalian cells. Bezlotoxumab does not bind to C. difficile toxin A.

Activity In Vitro

Bezlotoxumab binds to an epitope on toxin B that is conserved across reported strains of C. difficile, although amino acid sequence variation within the epitope does occur. In vitro studies in cell-based assays using Vero cells or Caco-2 cells, suggest that bezlotoxumab neutralizes the toxic effects of toxin B.

12.6 Immunogenicity

The observed incidence of anti-drug antibodies (ADA) is highly dependent on the sensitivity and specificity of the assay. Differences in assay methods preclude meaningful comparisons of the incidence of ADA in the studies described below with the incidence of ADA in other studies, including those of ZINPLAVA or of other bezlotoxumab products.

Following treatment with a single dose of ZINPLAVA in:

- Trial 1 and Trial 2 [see Clinical Studies (14)], none of the 710 evaluable adult patients with CDI developed anti-bezlotoxumab antibodies (referred to as ADA) through 12 weeks post-treatment.
- Trial 3 [see Adverse Reactions (6.1)], 2 of the 100 evaluable pediatric patients with CDI developed ADA through 12 weeks post-treatment.

Because of the low occurrence of ADA, the effect of these ADA on the pharmacokinetics, pharmacodynamics, safety and/or effectiveness of ZINPLAVA is unknown.

13 NONCLINICAL TOXICOLOGY

13.1 Carcinogenesis, Mutagenesis, Impairment of Fertility

No studies have been performed to test the potential of bezlotoxumab for carcinogenicity or genotoxicity.

Fertility studies have not been conducted with bezlotoxumab.

14 CLINICAL STUDIES

Clinical Trials in Adults

The safety and efficacy of ZINPLAVA were investigated in two randomized, double-blind, placebo-controlled, multicenter, Phase 3 trials (Trial 1 and Trial 2) in patients receiving Standard of Care antibacterial drugs for treatment of CDI (SoC).

Randomization was stratified by SoC (metronidazole, vancomycin, or fidaxomicin) and hospitalization status (inpatient vs. outpatient) at the time of study entry.

Enrolled patients were 18 years of age or older and had a confirmed diagnosis of CDI, which was defined as diarrhea (passage of 3 or more loose bowel movements in 24 or fewer hours) and a positive stool test for toxigenic C. difficile from a stool sample collected no more than 7 days before study entry. Patients were excluded if surgery for CDI was planned, or if they had uncontrolled chronic diarrheal illness. Patients received a 10- to 14-day course of oral SoC and a single infusion of ZINPLAVA or placebo was administered during the course of SoC. Patients on oral vancomycin or oral fidaxomicin could have also received intravenous metronidazole. Choice of SoC was at the discretion of the health care provider. The day of the infusion of ZINPLAVA or placebo in relation to the start of SoC ranged from the day prior to the start of SoC to 14 days after the start of SoC with the median being day 3 of SoC.

In Trial 1, 403 patients were randomized to receive ZINPLAVA and 404 patients were randomized to receive placebo. In Trial 2, 407 subjects were randomized to receive ZINPLAVA and 399 patients were randomized to receive placebo. The Full Analysis Set (FAS) was a subset of all randomized subjects with exclusions for: (i) not receiving infusion of study medication; (ii) not having a positive local stool test for toxigenic C. difficile; (iii) not receiving protocol defined standard of care therapy within a 1 day window of the infusion. The baseline characteristics of the 1554 patients randomized to ZINPLAVA or placebo in the FAS were similar across treatment arms and in Trial 1 and Trial 2. The median age was 65 years, 85% were white, 57% were female, and 68% were inpatients. A similar proportion of patients received oral metronidazole (48%) or oral vancomycin (48%) and 4% of the patients received oral fidaxomicin as their SoC.

The following risk factors associated with a high risk of CDI recurrence or CDI-related adverse outcomes were present in the study population: 51% were ≥65 years of age, 39% received one or more systemic antibacterial drugs (during the 12-week follow-up period), 28% had one or more episodes of CDI within the six months prior to the episode under treatment (15% had two or more episodes prior to the episode under treatment), 21% were immunocompromised and 16% presented at study entry with clinically severe CDI (as defined by a Zar score of ≥2^1). A hypervirulent strain (ribotypes 027, 078 or 244) was isolated in 22% of patients who had a positive baseline culture, of which 87% (189 of 217 strains) were ribotype 027.

Patients were assessed for clinical cure of the presenting CDI episode, defined as no diarrhea for 2 consecutive days following the completion of a ≤14 day SoC regimen. Patients who achieved clinical cure were then assessed for recurrence of CDI through 12 weeks following administration of the infusion of ZINPLAVA or placebo. CDI recurrence was defined as the development of a new episode of diarrhea associated with a positive stool test for toxigenic C. difficile following clinical cure of the presenting CDI episode. Sustained clinical response was defined as clinical cure of the presenting CDI episode and no CDI recurrence through 12 weeks after infusion. Table 2 contains the results for Trial 1 and Trial 2.

Table 2: Efficacy Results Through 12 Weeks After Infusion (Trial 1 and Trial 2, Full Analysis Set [Full Analysis Set = a subset of all randomized subjects with exclusions for: (i) did not receive infusion of study medication; (ii) did not have a positive local stool test for toxigenic C. difficile; (iii) did not receive protocol defined standard of care therapy within a 1 day window of the infusion])
Trial |  | ZINPLAVA with SoC [SoC = Standard of Care antibacterial drugs (metronidazole or vancomycin or fidaxomicin) for CDI] | Placebo with SoC | Adjusted Difference (95% CI) [Adjusted difference of ZINPLAVA-placebo (95% confidence interval) based on Miettinen and Nurminen method stratified by SoC antibacterial drugs (metronidazole vs. vancomycin vs. fidaxomicin) and hospitalization status (inpatient vs. outpatient).]
 |  | n (%) | n (%)
1 |  | N=386 | N=395
 | Sustained clinical response | 232 (60.1) | 218 (55.2) | 4.8 (-2.1, 11.7)
 | Reasons for failure to achieve sustained clinical response:
 | Clinical failure | 87 (22.5) | 68 (17.2)
 | Recurrence | 67 (17.4) | 109 (27.6)
2 |  | N=395 | N=378
 | Sustained clinical response | 264 (66.8) | 197 (52.1) | 14.6 (7.7, 21.4)
 | Reasons for failure to achieve sustained clinical response:
 | Clinical failure | 69 (17.5) | 84 (22.2)
 | Recurrence | 62 (15.7) | 97 (25.7)
n (%) = Number (percentage) of subjects in the analysis population meeting the criteria for endpoint
N = Number of subjects included in the analysis population

In Trial 1, the clinical cure rate of the presenting CDI episode was lower in the ZINPLAVA arm as compared to the placebo arm and in Trial 2, the clinical cure rate was lower in the placebo arm compared to the ZINPLAVA arm. Patients in the ZINPLAVA and placebo arms who did not achieve clinical cure of the presenting CDI episode (no diarrhea for 2 consecutive days following the completion of a ≤14 day SoC regimen) received a mean of 18 to 19 days of SoC and had a mean of 4 additional days of diarrhea following completion of SoC. Additional analyses showed that by 3 weeks post study drug infusion the clinical cure rates of the presenting CDI episode were similar between treatment arms.

Efficacy results in patients at high risk for CDI recurrence (i.e., patients aged 65 years and older, with a history of CDI in the past 6 months, immunocompromised state, severe CDI at presentation, or C. difficile ribotype 027) were consistent with the efficacy results in the overall trial population in Trials 1 and 2.

15 REFERENCES

1. Zar FA, Bakkanagari SR, Moorthi KM, Davis MB. A comparison of vancomycin and metronidazole for the treatment of Clostridium difficile-associated diarrhea, stratified by disease severity. Clin Infect Dis 2007;45(3):302-7.

16 HOW SUPPLIED/STORAGE AND HANDLING

ZINPLAVA Injection: is a sterile, preservative-free, clear to moderately opalescent, colorless to pale yellow solution and is supplied in the following packaging configuration:

Carton (NDC 0006-3025-00) containing one (1) single-dose vial of ZINPLAVA 1,000 mg/40 mL (25 mg/mL).

STORAGE AND HANDLING

Store in a refrigerator, 2ºC to 8ºC (36ºF to 46ºF) in original carton to protect from light. Do Not Freeze. Do Not Shake.

17 PATIENT COUNSELING INFORMATION

Advise the patient to read the FDA-approved patient labeling (Patient Information).

Concurrent Antibacterial Therapy

Advise patients, their families, or caregivers that ZINPLAVA does not take the place of their antibacterial treatment for their CDI infection. They must continue their antibacterial treatment as directed [see Indications and Usage (1) and Dosage and Administration (2.1)].

Manufactured by: Merck Sharp & Dohme LLC
Rahway, NJ 07065, USA
U.S. License No. 0002

At:
MSD Ireland (Carlow)
County Carlow, Ireland

For patent information: www.msd.com/research/patent

Copyright © 2016-2023 Merck & Co., Inc., Rahway, NJ, USA, and its affiliates.
All rights reserved.

uspi-mk6072-iv-2305r002

Patient Information
ZINPLAVA™ (zin-PLAH-va)
(bezlotoxumab)
injection, for intravenous use

What is ZINPLAVA?
ZINPLAVA is a prescription medicine used to help decrease the risk of C-diff (Clostridioides difficile infection) from coming back in adults and children 1 year of age and older who are taking an antibiotic for C-diff and who have a high risk of C-diff coming back.
ZINPLAVA is not used to treat C-diff and is not an antibiotic. ZINPLAVA should only be used along with the antibiotic that you are taking to treat C-diff. Keep taking your antibiotic for your C-diff as directed by your doctor.
It is not known if ZINPLAVA is safe and effective in children under 1 year of age.

Before receiving ZINPLAVA, tell your doctor about all of your medical conditions, including if you:

- have or have had congestive heart failure (CHF).
- are pregnant or trying to get pregnant. It is not known if ZINPLAVA will harm your unborn baby. You and your doctor should decide together if you will receive ZINPLAVA.
- are breastfeeding or plan to breastfeed. It is not known if ZINPLAVA passes into your breast milk. You and your doctor should decide together if you will receive ZINPLAVA.

Tell your doctor about all of the medicines you take, including prescription and over-the-counter medicines, vitamins, and herbal supplements.

How will I receive ZINPLAVA?

- You will receive ZINPLAVA into your vein through an IV (intravenously).
- You do not need to do anything to prepare for receiving ZINPLAVA.
- You will receive ZINPLAVA in 1 dose and it will take about 1 hour.
- If you miss your appointment, call your doctor right away to reschedule it.

What are the possible side effects of ZINPLAVA?
ZINPLAVA may cause serious side effects, including:

- Heart failure. Heart failure may happen in people who receive ZINPLAVA and can be serious. People with a history of congestive heart failure (CHF) who received ZINPLAVA had a higher rate of heart failure and death than those who did not receive ZINPLAVA.

Common side effects of ZINPLAVA:
The most common side effects that may happen on the day of or the day after receiving ZINPLAVA include:

- nausea
- headache
- fever
- feeling tired

- shortness of breath
- feeling dizzy
- high blood pressure

The most common side effects that may happen up to four weeks after receiving ZINPLAVA include:

- nausea
- fever

- headache

If you have any side effect that bothers you or does not go away, tell your doctor.
These are not all the possible side effects of ZINPLAVA. For more information, ask your doctor or pharmacist.
Call your doctor for medical advice about side effects. You may report side effects to FDA at 1-800-FDA-1088.

General information about the safe and effective use of ZINPLAVA.
Medicines are sometimes prescribed for purposes other than those listed in a Patient Information leaflet. You can ask your pharmacist or doctor for information about ZINPLAVA that is written for health professionals.

What are the ingredients in ZINPLAVA?
The active ingredient is: bezlotoxumab
The inactive ingredients are: citric acid monohydrate, diethylenetriaminepentaacetic acid, polysorbate 80, sodium chloride, sodium citrate dihydrate, and water for injection, USP. ZINPLAVA may also contain sodium hydroxide.
For more information, call the company that makes ZINPLAVA, at 1-800-444-2080, or go to the website – www.ZINPLAVA.com. You can also find the full prescribing information written for health professionals at www.ZINPLAVA.com
Manufactured by: Merck Sharp & Dohme LLC
Rahway, NJ 07065, USA
U.S. License No. 0002
At:
MSD Ireland (Carlow)
County Carlow, Ireland
For patent information: www.msd.com/research/patent
Copyright © 2016-2023 Merck & Co., Inc., Rahway, NJ, USA, and its affiliates
All rights reserved.
usppi-mk6072-iv-2305r002

This Patient Information has been approved by the U.S. Food and Drug Administration.

Issued: 5/2023

PRINCIPAL DISPLAY PANEL - 1,000 mg/40 mL Vial Carton

NDC 0006-3025-00

Zinplava™
(bezlotoxumab)
Injection

1,000 mg /40 mL
(25 mg/mL)

For Intravenous Infusion Only

Requires dilution prior to administration.

Rx only

Single-dose vial. Discard unused portion.